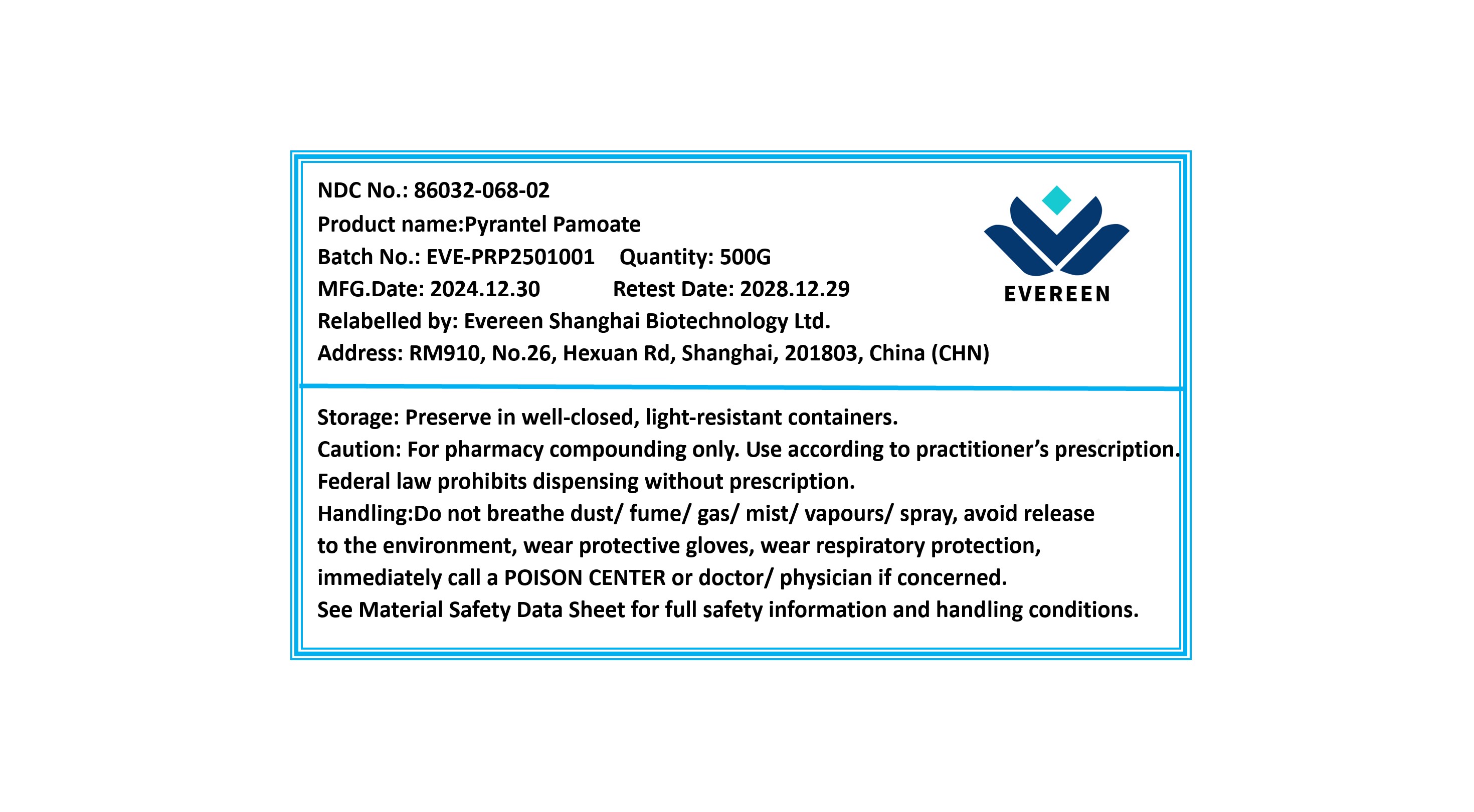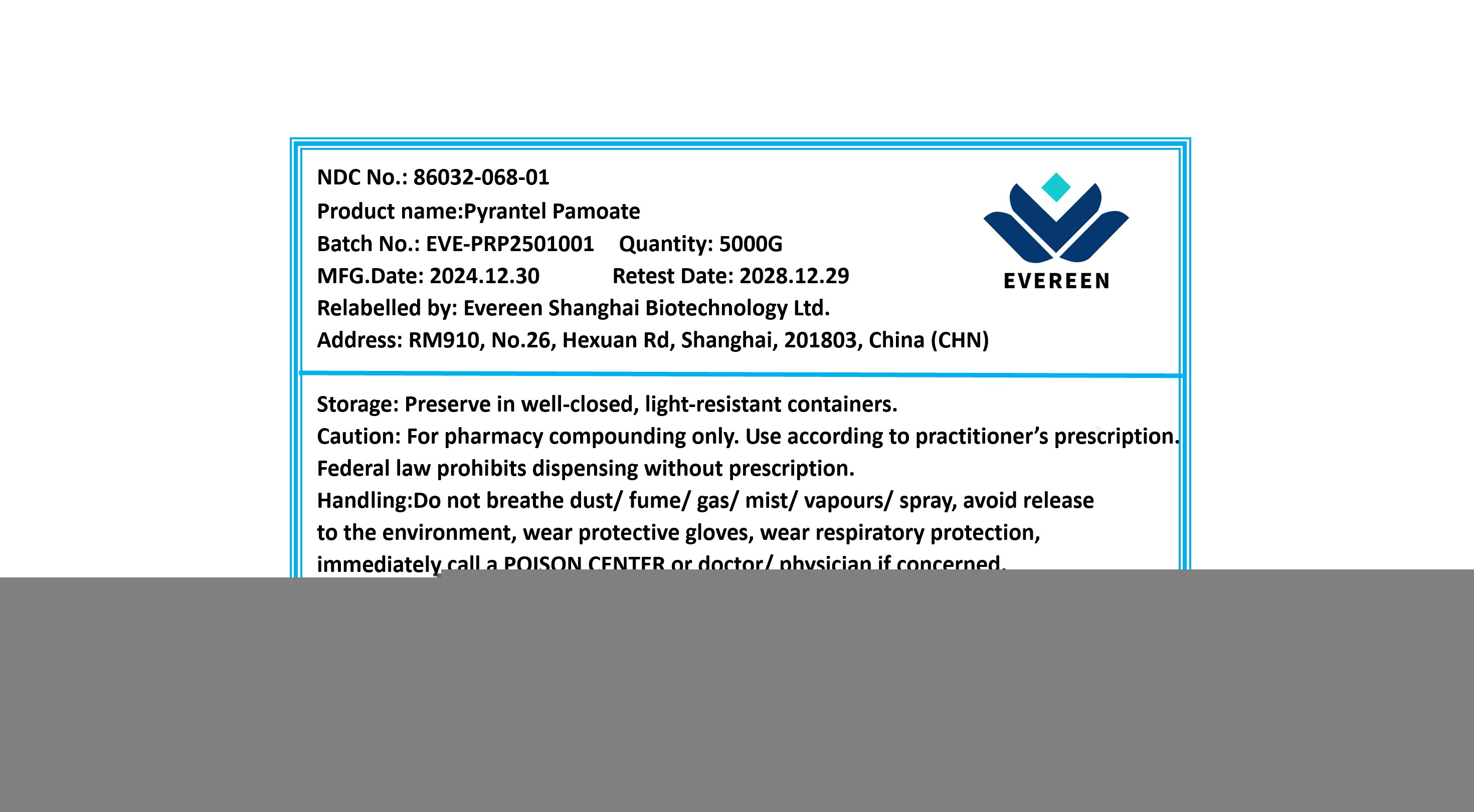 DRUG LABEL: Pyrantel Pamoate
NDC: 86032-068 | Form: POWDER
Manufacturer: Evereen Shanghai Biotechnology Ltd.
Category: other | Type: BULK INGREDIENT - ANIMAL DRUG
Date: 20260108

ACTIVE INGREDIENTS: PYRANTEL PAMOATE 1 g/1 g

Pyrantel Pamoate